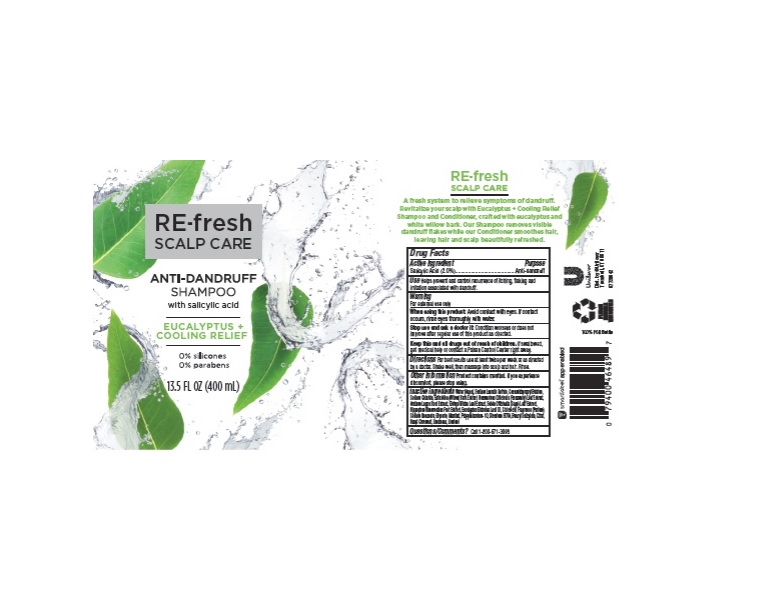 DRUG LABEL: RE-fresh Scalp Care
NDC: 64942-1635 | Form: SHAMPOO
Manufacturer: Conopco, Inc. d/b/a/ Unilever
Category: otc | Type: HUMAN OTC DRUG LABEL
Date: 20221207

ACTIVE INGREDIENTS: SALICYLIC ACID 2 g/100 mL
INACTIVE INGREDIENTS: WATER; SODIUM LAURETH SULFATE; COCAMIDOPROPYL BETAINE; SODIUM CHLORIDE; ARCTIUM LAPPA ROOT; GINKGO; EUCALYPTUS OIL; CITRIC ACID MONOHYDRATE; SODIUM BENZOATE; GLYCERIN; MENTHOL; POLYQUATERNIUM-10 (1000 MPA.S AT 2%); EDETATE DISODIUM ANHYDROUS; BENZYL SALICYLATE; CITRAL; .ALPHA.-HEXYLCINNAMALDEHYDE; LIMONENE, (+)-; LINALOOL, (+/-)-

RE-fresh Scalp Care Eucalyptus + Cooling Relief Anti-Dandruff Shampoo

RE-FRESH SCALP CARE EUCALYPTUS + COOLING RELIEF ANTI-DANDRUFF SHAMPOO - salicylic acid liquid

RE-fresh Scalp Care Eucalyptus + Cooling Relief Anti-Dandruff Shampoo

Drug Facts

Active ingredient

Salicylic Acid (2.0%)

Purpose

Anti-dandruff

Use

• Helps prevent and control recurrence of itching, flaking and irritation associated with dandruff.

Warnings

For external use only
When using this product Avoid contact with eyes. If contact occurs, rinse eyes thoroughly with water.
Stop use and ask a doctor if: Condition worsens or does not improve after regular use of this product as directed.

KEEP OUT OF REACH OF CHILDREN

Keep this and all drugs out of reach of children. If swallowed, get medical help or contact a Poison Control Center right away.

Directions

For best results use at least twice per week or as directed by a doctor. Massage into scalp and hair. Rinse.

Other Information

Product contains menthol. If you experience discomfort, please stop using.

Inactive Ingredients

Water (Aqua), Sodium Laureth Sulfate, Cocamidopropyl Betaine, Sodium Chloride, Salix Alba (Willow) Bark Extract, Rosmarinus Officinalis (Rosemary) Leaf Extract, Arctium Lappa Root Extract, Ginkgo Biloba Leaf Extract, Salvia Officinalis (Sage) Leaf Extract, Hippophae Rhamnoides Fruit Extract, Eucalyptus Globulus Leaf Oil, Citric Acid, Fragrance (Parfum), Sodium Benzoate, Glycerin, Menthol, Polyquaternium-10, Disodium EDTA, Benzyl Salicylate. Citral, Hexyl Cinnamal, Limonene, Linalool.

Questions, comments?

Call 1-800-761-3683